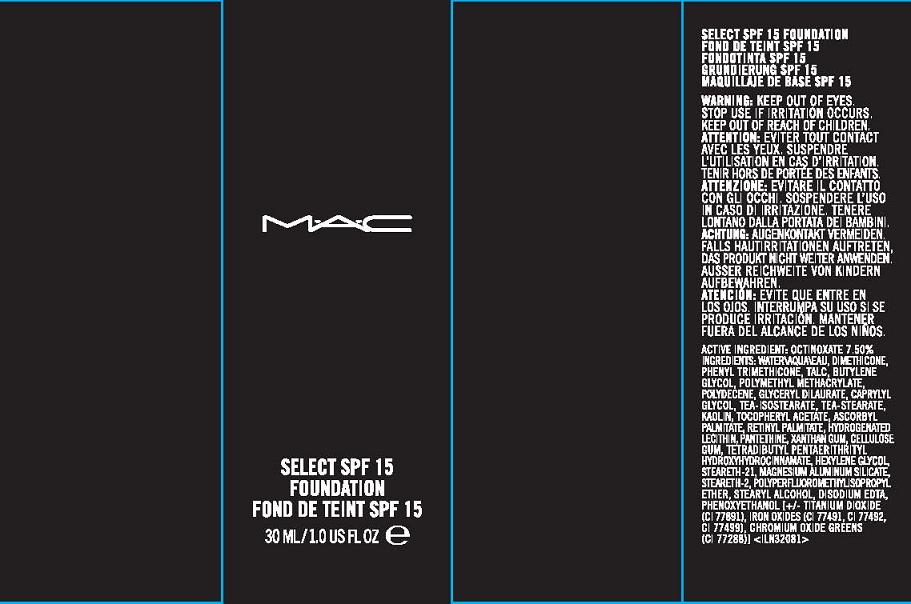 DRUG LABEL: SELECT
NDC: 40046-0052 | Form: CREAM
Manufacturer: MAKEUP ART COSMETICS
Category: otc | Type: HUMAN OTC DRUG LABEL
Date: 20111005

ACTIVE INGREDIENTS: OCTINOXATE 7.5 mL/100 mL
INACTIVE INGREDIENTS: WATER; DIMETHICONE; PHENYL TRIMETHICONE; TALC; BUTYLENE GLYCOL; CAPRYLYL GLYCOL; TROLAMINE; STEARIC ACID; KAOLIN; ALPHA-TOCOPHEROL ACETATE; ASCORBYL PALMITATE; VITAMIN A PALMITATE; HYDROGENATED SOYBEAN LECITHIN; PANTETHINE; XANTHAN GUM; CARBOXYMETHYLCELLULOSE SODIUM; HEXYLENE GLYCOL; STEARETH-21; MAGNESIUM ALUMINUM SILICATE; STEARYL ALCOHOL; EDETATE DISODIUM; PHENOXYETHANOL; TITANIUM DIOXIDE; FERRIC OXIDE RED; CHROMIC OXIDE

ACTIVE INGREDIENT: OCTINOXATE 7.50%

INACTIVE INGREDIENT

INACTIVE INGREDIENTS: WATER [] DIMETHICONE [] PHENYL TRIMETHICONE [] TALC [] BUTYLENE GLYCOL [] POLYMETHYL METHACRYLATE [] POLYDECENE [] GLYCERYL DILAURATE [] CAPRYLYL GLYCOL [] TEA-ISOSTEARATE [] TEA-STEARATE [] KAOLIN [] TOCOPHERYL ACETATE [] ASCORBYL PALMITATE [] RETINYL PALMITATE [] HYDROGENATED LECITHIN [] PANTETHINE [] XANTHAN GUM [] CELLULOSE GUM [] TETRADIBUTYL PENTAERITHRITYL HYDROXYHYDROCINNAMATE [] HEXYLENE GLYCOL [] STEARETH-21 [] MAGNESIUM ALUMINUM SILICATE [] STEARETH-2 [] POLYPERFLUOROMETHYLISOPROPYL ETHER [] STEARYL ALCOHOL [] DISODIUM EDTA [] PHENOXYETHANOL [] [+/- TITANIUM DIOXIDE (CI 77891) [] IRON OXIDES (CI 77491, CI 77492, CI 77499) [] CHROMIUM OXIDE GREENS (CI 77288)]

WARNINGS

WARNING: KEEP OUT OF EYES. STOP USE IF IRRITATION OCCURS. KEEP OUT OR REACH OF CHILDREN.

PACKAGE LABEL

MAC
SELECT
SPF 15
FOUNDATION
1.0 FL/OZ/ 30 ML
DISTR. MAKEUP ART COSMETICS
ONTARIO, CANADA